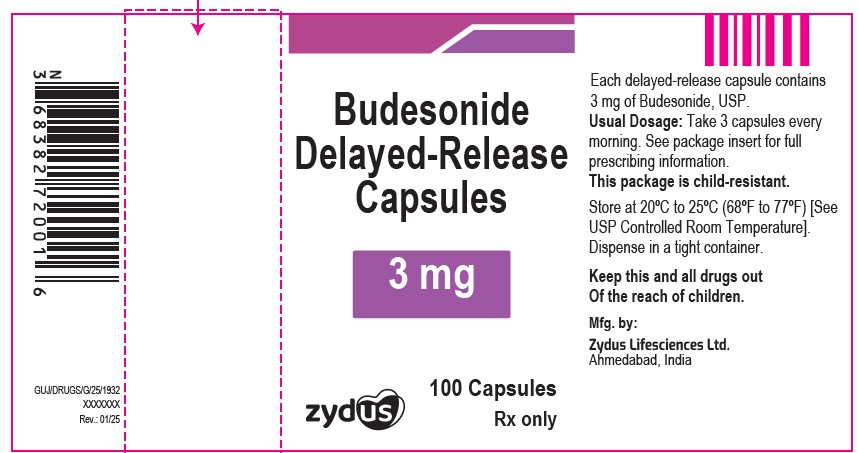 DRUG LABEL: budesonide
NDC: 70771-1075 | Form: CAPSULE, COATED PELLETS
Manufacturer: Zydus Lifesciences Limited
Category: prescription | Type: HUMAN PRESCRIPTION DRUG LABEL
Date: 20250212

ACTIVE INGREDIENTS: BUDESONIDE 3 mg/1 1
INACTIVE INGREDIENTS: ACETYLTRIBUTYL CITRATE; ALCOHOL; AMMONIA; BUTYL ALCOHOL; DIMETHICONE; ETHYLCELLULOSES; FERRIC OXIDE RED; FERRIC OXIDE YELLOW; FERROSOFERRIC OXIDE; GELATIN; ISOPROPYL ALCOHOL; METHACRYLIC ACID AND ETHYL ACRYLATE COPOLYMER; POLYSORBATE 80; POTASSIUM HYDROXIDE; PROPYLENE GLYCOL; SHELLAC; SODIUM LAURYL SULFATE; SUCROSE; TALC; TITANIUM DIOXIDE; TRIETHYL CITRATE; WATER

BUDESONIDE DELAYED-RELEASE CAPSULES

PACKAGE LABEL.PRINCIPAL DISPLAY PANEL

NDC 70771-1075-1 in bottle of 100 capsules

Budesonide Delayed-Release Capsules 3 mg

100 capsules

Rx only